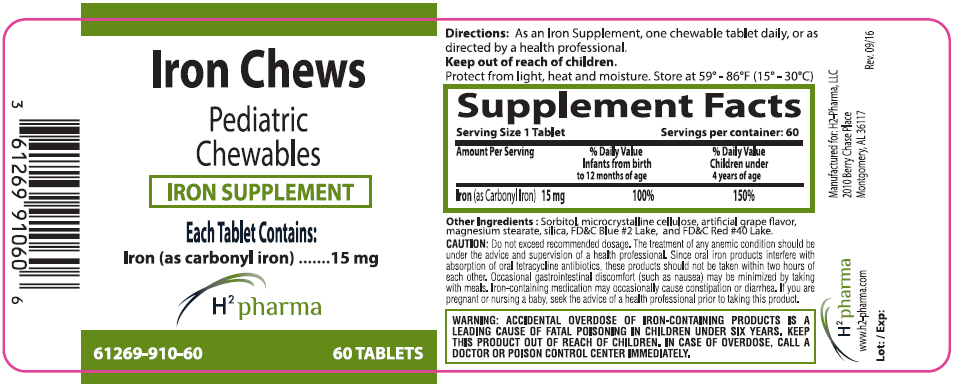 DRUG LABEL: Iron Chews
NDC: 61269-910 | Form: TABLET, CHEWABLE
Manufacturer: H2-Pharma, LLC
Category: other | Type: DIETARY SUPPLEMENT
Date: 20220728

ACTIVE INGREDIENTS: IRON PENTACARBONYL 15 mg/1 1
INACTIVE INGREDIENTS: SORBITOL; MICROCRYSTALLINE CELLULOSE; MAGNESIUM STEARATE; SILICON DIOXIDE; FD&C BLUE NO. 2; FD&C RED NO. 40

Iron Chews

Directions

As an Iron Supplement, one chewable tablet daily, or as directed by a health professional.

Keep out of reach of children.

Protect from light, heat and moisture. Store at 59° - 86°F (15° - 30°C)

STATEMENT OF IDENTITY

Supplement Facts
Serving Size 1 Tablet | Servings per container: 60
Amount Per Serving | % Daily Value Infants from birth to 12 months of age | % Daily Value Children under 4 years of age
Iron (as Carbonyl Iron) 15 mg | 100% | 150%

Other Ingredients : Sorbitol, microcrystalline cellulose, artificial grape flavor, magnesium stearate, silica, FD&C Blue #2 Lake, and FD&C Red #40 Lake.

CAUTION

Do not exceed recommended dosage. The treatment of any anemic condition should be under the advice and supervision of a health professional. Since oral iron products interfere with absorption of oral tetracycline antibiotics, these products should not be taken within two hours of each other. Occasional gastrointestinal discomfort (such as nausea) may be minimized by taking with meals. Iron-containing medication may occasionally cause constipation or diarrhea. If you are pregnant or nursing a baby, seek the advice of a health professional prior to taking this product.

WARNING

ACCIDENTAL OVERDOSE OF IRON-CONTAINING PRODUCTS IS A LEADING CAUSE OF FATAL POISONING IN CHILDREN UNDER SIX YEARS. KEEP THIS PRODUCT OUT OF REACH OF CHILDREN. IN CASE OF OVERDOSE, CALL A DOCTOR OR POISON CONTROL CENTER IMMEDIATELY.

HEALTH CLAIM

H^2 pharma
www.h2-pharma.com

Rev. 09/16

PRINCIPAL DISPLAY PANEL - 15 mg Tablet Bottle Label

Iron Chews

Pediatric
Chewables

IRON SUPPLEMENT

Each Tablet Contains:
Iron (as carbonyl iron) .......15 mg

H^2 pharma

61269-910-60
60 TABLETS